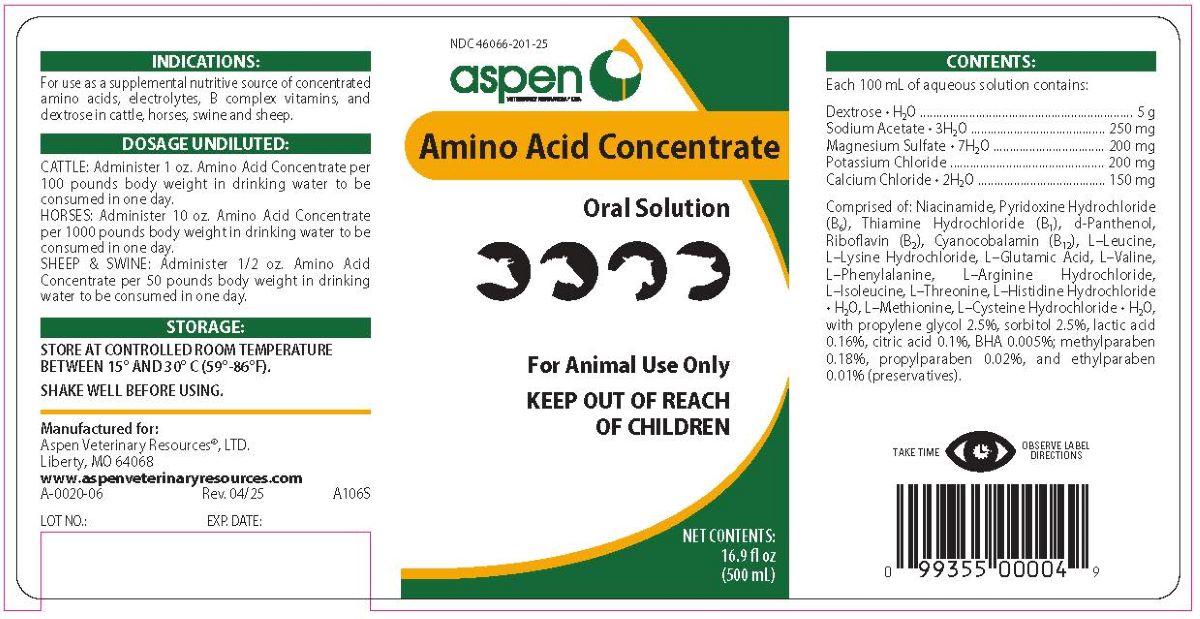 DRUG LABEL: AMINO ACID
NDC: 46066-201 | Form: CONCENTRATE
Manufacturer: Aspen Veterinary Resources, Ltd.
Category: animal | Type: OTC ANIMAL DRUG LABEL
Date: 20250428

ACTIVE INGREDIENTS: CALCIUM CHLORIDE ANHYDROUS 150 mg/100 mL; DEXTROSE MONOHYDRATE 5 g/100 mL; MAGNESIUM SULFATE HEPTAHYDRATE 200 mg/100 mL; POTASSIUM CHLORIDE 200 mg/100 mL; SODIUM ACETATE ANHYDROUS 250 mg/100 mL
INACTIVE INGREDIENTS: ACETATE ION; DEXPANTHENOL; PHENYLALANINE; PROPYLPARABEN; PYRIDOXINE HYDROCHLORIDE; RIBOFLAVIN 5'-PHOSPHATE SODIUM; SORBITOL; THIAMINE HYDROCHLORIDE; THREONINE; VALINE; ANHYDROUS CITRIC ACID; CYSTEINE HYDROCHLORIDE; ETHYLPARABEN; GLUTAMIC ACID; HISTIDINE MONOHYDROCHLORIDE MONOHYDRATE; ISOLEUCINE; LACTIC ACID; LEUCINE; ARGININE HYDROCHLORIDE; LYSINE HYDROCHLORIDE; METHIONINE; METHYLPARABEN; NIACINAMIDE; PROPYLENE GLYCOL; WATER

AMINO ACID CONCENTRATE

INDICATIONS AND USAGE

Oral Solution

For Animal Use Only

KEEP OUT OF REACH OF CHILDREN

INDICATIONS

For use as a supplemental nutritive source of concentrated amino acids, electrolytes, B complex vitamins, and dextrose in cattle, horses, swine and sheep.

DOSAGE UNDILUTED

CATTLE: Administer 1 oz. Amino Acid Concentrate per
100 pounds body weight in drinking water to be
consumed in one day.
HORSES: Administer 10 oz. Amino Acid Concentrate
per 1000 pounds body weight in drinking water to be
consumed in one day.
SHEEP & SWINE: Administer 1/2 oz. Amino Acid
Concentrate per 50 pounds body weight in drinking
water to be consumed in one day.

STORAGE AND HANDLING

Store between between 15° and 30°C (59°-86°F)

SHAKE WELL BEFORE USING.

TAKE TIME OBSERVE LABEL DIRECTIONS.

CONTENTS

Each 100 mL of aqueous solution contains:

Dextrose • H2O .......................... 5 g
Sodium Acetate • 3H2O ........ 250 mg
Magnesium Sulfate • 7H2O ... 200 mg
Potassium Chloride .............. 200 mg
Calcium Chloride • 2H2O .......150 mg

Comprised of : Niacinamide, Pyridoxine Hydrochloride (B6), Thiamine Hydrochloride (B1), d-Panthenol, Riboflavin (B2), Cyanocobalamin (B12), L-Leucine, L-Lysine Hydrochloride, L-Glutamic Acid, L-Valine, L-Phenylalanine, L-Arginine Hydrochloride, L-Isoleucine, L-Threonine, L-Histidine Hydrochloride • H2O, L-Methionine, L-Cysteine Hydrochloride • H2O, with propylne glycol 2.5%, sorbitol 2.5%, lactic acid 0.16%, citric acid 0.1%, BHA 0.005%, methylparaben 0.18%, propylparaben 0.02%, and ehtylparaben 0.01% (preservatives).